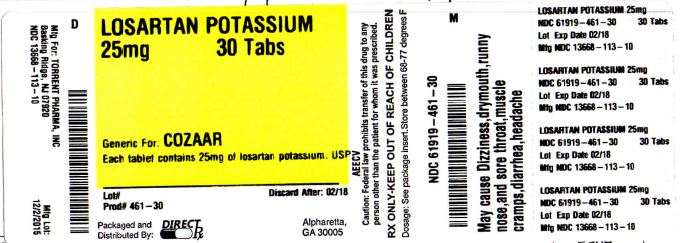 DRUG LABEL: LOSARTAN POTASSIUM
NDC: 61919-461 | Form: TABLET
Manufacturer: DirectRX
Category: prescription | Type: HUMAN PRESCRIPTION DRUG LABEL
Date: 20151203

ACTIVE INGREDIENTS: LOSARTAN POTASSIUM 25 mg/1 1
INACTIVE INGREDIENTS: CELLULOSE, MICROCRYSTALLINE; HYDROXYPROPYL CELLULOSE (TYPE H); HYPROMELLOSE 2910 (6 MPA.S); ANHYDROUS LACTOSE; COLLOIDAL SILICON DIOXIDE; MAGNESIUM STEARATE; STARCH, PREGELATINIZED CORN; TALC; TITANIUM DIOXIDE

LOSARTAN POTASSIUM

Boxed Warning

fetal toxicity

When pregnancy is detected, discontinue losartan potassium tablets as soon as possible.
Drugs that act directly on the rennin-angiotensin system can cause injury and death to the developing fetus. See WARNINGS, Fetal Toxicity.